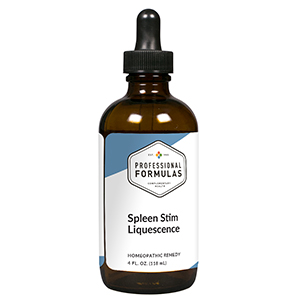 DRUG LABEL: Spleen Stim Liquescence
NDC: 63083-3028 | Form: LIQUID
Manufacturer: Professional Complementary Health Formulas
Category: homeopathic | Type: HUMAN OTC DRUG LABEL
Date: 20190815

ACTIVE INGREDIENTS: QUERCUS ROBUR WOOD 4 [hp_X]/118 mL; CEANOTHUS AMERICANUS LEAF 6 [hp_X]/118 mL; BOS TAURUS SPLEEN 6 [hp_X]/118 mL; HELIANTHUS ANNUUS FLOWERING TOP 6 [hp_X]/118 mL; SODIUM CHLORIDE 6 [hp_X]/118 mL
INACTIVE INGREDIENTS: ALCOHOL; WATER

T28

ACTIVE INGREDIENTS

Quercus robur 4X
Ceanothus americanus 6X
Spleen 6X
Helianthus annuus 6X, 12X
Natrum muriaticum 6X, 12X, 30X

QUESTIONS

Professional Formulas

PO Box 2034 Lake Oswego, OR 97035

INDICATIONS

For the temporary relief of mild abdominal discomfort, lack of appetite or feeling of fullness, shortness of breath, weakness, fatigue, or feelings of discomfort or uneasiness.*

PURPOSE

*Claims based on traditional homeopathic practice, not accepted medical evidence. Not FDA evaluated.

WARNINGS

Severe or persistent symptoms may be a sign of a serious condition. Consult a doctor promptly if you have pain in your left upper abdomen, especially if it's severe or the pain gets worse when you take a deep breath. Keep out of the reach of children. In case of overdose, get medical help or contact a poison control center right away. If pregnant or breastfeeding, ask a healthcare professional before use.

Keep out of the reach of children.

PREGNANCY OR BREAST FEEDING

If pregnant or breastfeeding, ask a healthcare professional before use.

DIRECTIONS

Place drops under tongue 30 minutes before/after meals. Adults and children 12 years and over: Take one full dropper up to 2 times per day. Consult a physician for use in children under 12 years of age.

OTHER INFORMATION

Tamper resistant. If seal is broken, do not use. After opening, close container tightly and store at room temperature away from heat.

INACTIVE INGREDIENTS

20% ethanol, purified water.

LABEL

Est 1985

Professional Formulas

Complementary Health

Spleen Stim Liquescence

Homeopathic Remedy

4 FL. OZ. (118 mL)